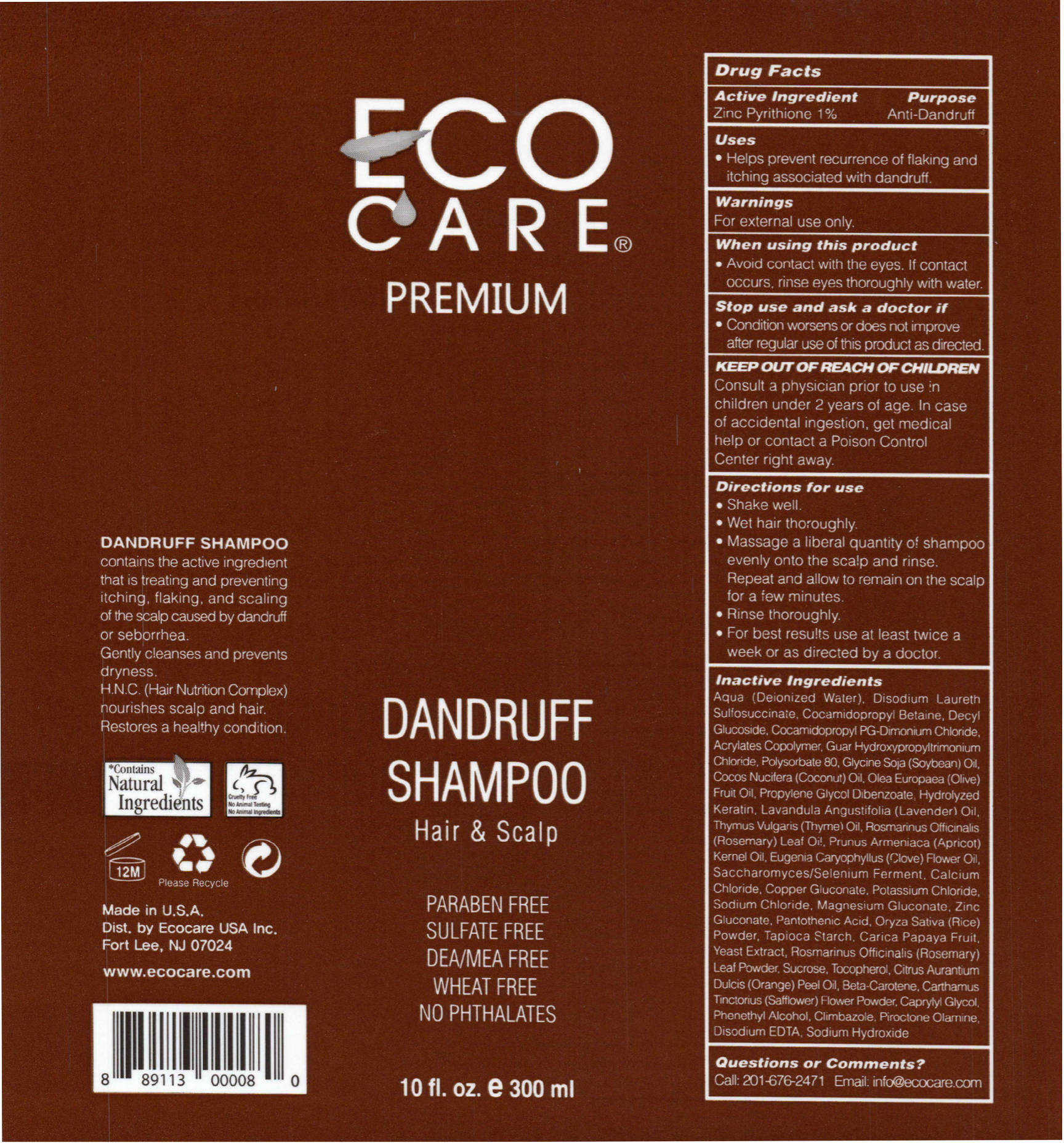 DRUG LABEL: Dandruff
NDC: 46607-112 | Form: SHAMPOO
Manufacturer: Ecocare
Category: otc | Type: HUMAN OTC DRUG LABEL
Date: 20200407

ACTIVE INGREDIENTS: PYRITHIONE ZINC 10.0 mg/100 mL
INACTIVE INGREDIENTS: DISODIUM 1-(LAURETH-2) SULFOSUCCINATE; COCAMIDOPROPYL BETAINE; DECYL GLUCOSIDE; COCAMIDOPROPYL PG-DIMONIUM CHLORIDE; GUAR HYDROXYPROPYLTRIMONIUM CHLORIDE (1.7 SUBSTITUENTS PER SACCHARIDE); AMINO ACIDS, HAIR KERATIN; ACRYLATE/ISOBUTYL METHACRYLATE/N-TERT-OCTYLACRYLAMIDE COPOLYMER (75000 MW); TOCOPHEROL; POLYSORBATE 80; PANTOTHENIC ACID; SOYBEAN OIL; CALCIUM CHLORIDE; COCONUT OIL; COPPER GLUCONATE; OLIVE OIL; WATER; PROPYLENE GLYCOL DIBENZOATE; POTASSIUM CHLORIDE; SUPEROXIDE DISMUTASE (SACCHAROMYCES CEREVISIAE); MANGANESE GLUCONATE; MAGNESIUM GLUCONATE; ZINC GLUCONATE; SODIUM CHLORIDE; OLEA EUROPAEA FRUIT VOLATILE OIL; MYRTUS COMMUNIS LEAF; LAVANDULA ANGUSTIFOLIA FLOWER; ORANGE PEEL; THYMUS VULGARIS LEAF; BETA CAROTENE; ROSMARINUS OFFICINALIS FLOWERING TOP OIL; SAFFLOWER; PRUNUS ARMENIACA LEAF; 4-METHYLPHENETHYL ALCOHOL; CLOVE LEAF OIL; ORYZA SATIVA WHOLE; CLIMBAZOLE; STARCH, TAPIOCA; PIROCTONE OLAMINE; CARICA PAPAYA WHOLE; DISODIUM EDTA-COPPER; YEAST; sodium hydroxide; ROSMARINUS OFFICINALIS FLOWER; SALVIA OFFICINALIS FLOWERING TOP; SUCROSE; CAPRYLYL GLYCOL; CITRIC ACID ACETATE; TRIMETHYLENEDIAMINETETRAACETIC ACID

Drug Facts

Active Ingredients Purpose

Zinc Pyrithione 0.95%..............................................................Anti-Dandruff

Purpose

Uses: Helps prevent recurrence of flaking and itching associated with dandruff.

Warnings

FOR EXTERNAL USE ONLY

When using this product

Avoid contact with the eyes. If contact occurs, rinse eyes thoroughly with water.

Stop use and ask a doctor if condition worsens or does not improve after regular use of this product as directed.

Keep out of reach of children

Dosage and Administration

- Shake well.
- Wet hair thoroughly.
- Massage a liberal quantity of shampoo evenly onto the scalp and rinse. Repeat and allow to remain on the scalp for a few minutes.
- Rinse throroughly.
- For best results use at least twice a week or as directed by a doctor.

Other Information

For external use only

Inactive Ingredients

Aqua (Deionized Water), Decyl Glucoside, Lauryl Glucoside, Coco Glucoside, Hydrolyzed Soy Protein, Guar Hydroxypropyltrimonium Chloride, Hydrolyzed Keratin, Tocopherol, Pantothenic Acid, Saccharomyces/Selenium Ferment, Calcium Chloride, Copper Gluconate, Potassium Chloride, Managanese Gluconate, Magnesium Gluconate, Zinc Gluconate, Sodium Chloride, Olea Europaea Fruit Oil, Myrtus Comunis Oil, Lavandula Angustifolia Oil, Thymus Vulgaris Oil, Rosmarinus Officinalis Leaf Oil, Prunus Armeniaca Kernal Oil, Eugenia Caryophyllus Flower Oil, Oryza Sativa Powder, Tapioca Starch, Carica Papayan Fruit, Yeast Extract, Rosmarinus Officinalis Leaf Powder, Salvia Officinalis Leaf Extract, Sucrose, Phenethyl Alcohol, Caprylyl Glycol, Citric Acid, Tetrasodium EDTA, Essential Oils Blend

Indications

Helps prevent recurrance of flaking and itching associated with dandruff.

Do Not Use

- Condition worsens or does not improve after regular use of this product as directed.

Ask a doctor

- Condition worsens or does not improve after regular use of this product as directed.

Directions

- Shake well.
- Wet hair thoroughly.
- Massage a liberal quantity of shampoo evenly onto the scalp and rinse. Repeat and allow to remain on the scalp for a few minutes.
- Rinse thoroughly.
- For best results use at least twice a week or as directed by a doctor.